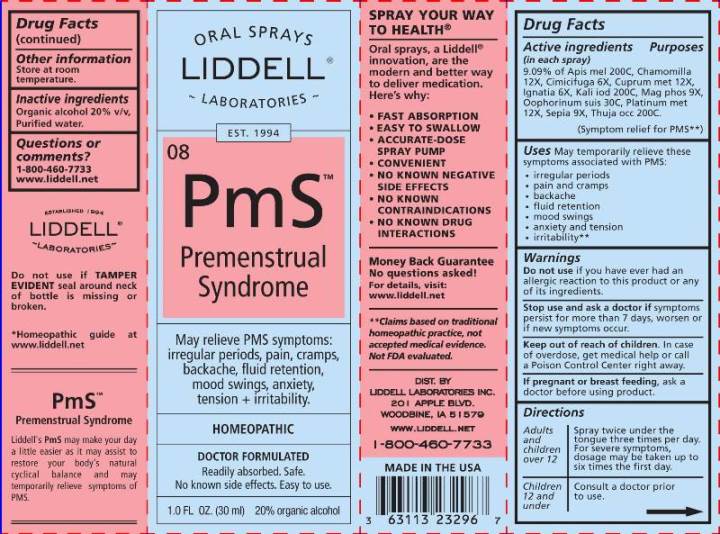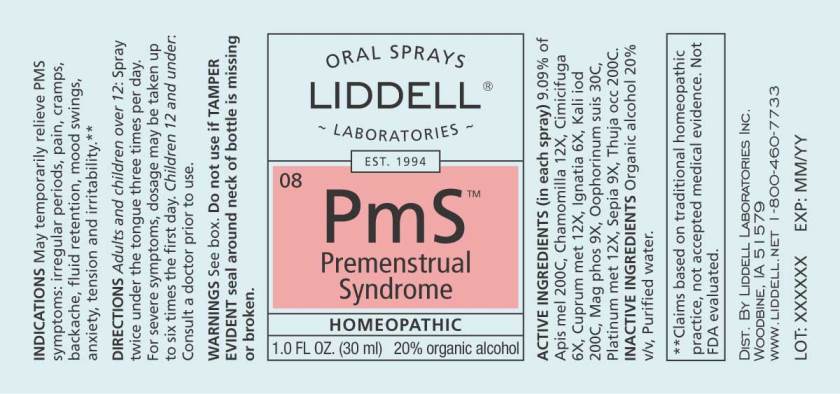 DRUG LABEL: PMS
NDC: 50845-0109 | Form: SPRAY
Manufacturer: Liddell Laboratories, Inc.
Category: homeopathic | Type: HUMAN OTC DRUG LABEL
Date: 20240701

ACTIVE INGREDIENTS: APIS MELLIFERA 200 [hp_C]/1 mL; MATRICARIA CHAMOMILLA WHOLE 12 [hp_X]/1 mL; BLACK COHOSH 6 [hp_X]/1 mL; COPPER 12 [hp_X]/1 mL; STRYCHNOS IGNATII SEED 6 [hp_X]/1 mL; POTASSIUM IODIDE 200 [hp_C]/1 mL; MAGNESIUM PHOSPHATE, DIBASIC TRIHYDRATE 9 [hp_X]/1 mL; SUS SCROFA OVARY 30 [hp_C]/1 mL; PLATINUM 12 [hp_X]/1 mL; SEPIA OFFICINALIS JUICE 9 [hp_X]/1 mL; THUJA OCCIDENTALIS LEAFY TWIG 200 [hp_C]/1 mL
INACTIVE INGREDIENTS: WATER; ALCOHOL

DRUG FACTS:

ACTIVE INGREDIENTS:

(in each drop): 9.09% of Apis mellifica 200C, Chamomilla 12X, Cimicifuga racemosa 6X, Cuprum metallicum 12X, Ignatia amara 6X, Kali iodatum 200C, Magnesia phosphorica 9X, Oophorinum (suis) 30C, Platinum metallicum 12X, Sepia 9X, Thuja occidentalis 200C.

USES:

May temporarily relieves these symptoms associated with PMS:

•irregular periods
•pain and cramps
•backache
•fluid retention
•mood swings
•anxiety and tension
•irritability**

**Claims based on traditional homeopathic practice, not accepted medical evidence. Not FDA evaluated.

WARNINGS:

Do not use if you have ever had an allergic reaction to this product or any of its ingredients.

Stop use and ask a doctor if symptoms persist, worsen or if new symptoms occur.

Keep out of reach of children. In case of overdose, get medical help or call a Poison Control Center right away.

If pregnant or breast feeding, ask a doctor before using product.

OTHER INFORMATION: Store at room temperature.

Do not use if TAMPER EVIDENT seal around neck of bottle is missing or broken.

DIRECTIONS:

Adults and children over 12: Spray twice under the tongue three times per day. For severe symptoms, dosage may be taken up to six times the first day.

Children 12 and under: Consult a doctor prior to use.

Keep out of reach of children. In case of overdose, get medical help or call a Poison Control Center right away.

INACTIVE INGREDIENTS:

Organic alcohol 20%v/v, Purified water

USES:

May temporarily relieves these symptoms associated with PMS:

•irregular periods
•pain and cramps
•backache
•fluid retention
•mood swings
•anxiety and tension
•irritability**

**Claims based on traditional homeopathic practice, not accepted medical evidence. Not FDA evaluated.

QUESTIONS:

LIDDELL LABORATORIES

201 APPLE BLVD.

WOODBINE, IA 51579

www.liddell.net

1-800-460-7733

PACKAGE LABEL DISPLAY:

ORAL SPRAYS
LIDDELL LABORATORIES
EST. 1994

^08PmS

Premenstrual

Syndrome

Relieves PMS symptoms:

irregular periods, pain, cramps,

backache, fluid retention,

mood swings, anxiety,

tension + irritability.

HOMEOPATHIC

DOCTOR FORMULATED
Readily absorbed. Safe.

No known side effects. Easy to use.
1.0 FL OZ (30 ml)